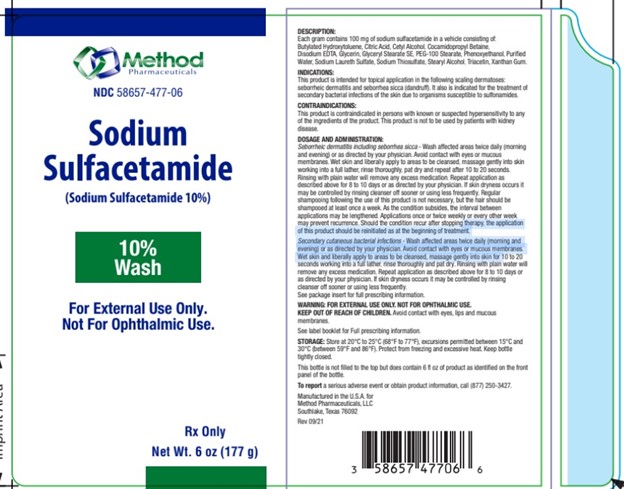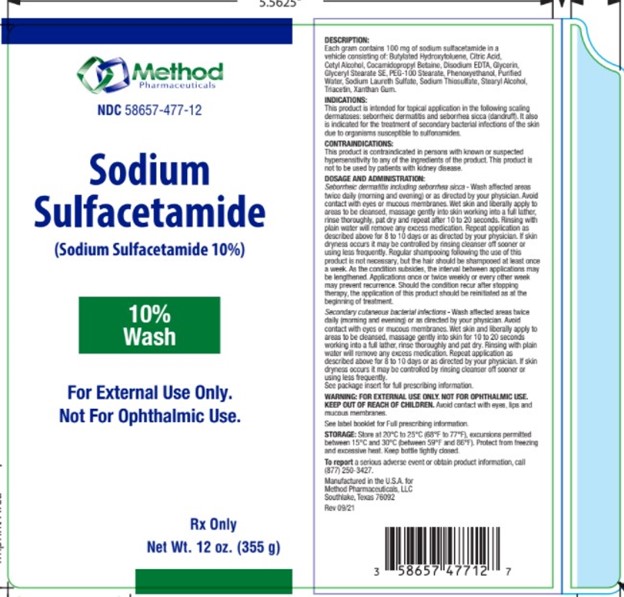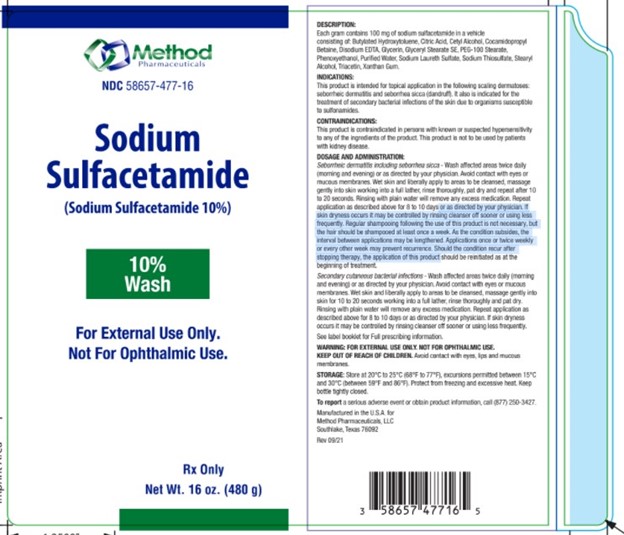 DRUG LABEL: Sodium Sulfacetamide
NDC: 58657-477 | Form: LIQUID
Manufacturer: Method Pharmaceuticals, LLC
Category: prescription | Type: HUMAN PRESCRIPTION DRUG LABEL
Date: 20260212

ACTIVE INGREDIENTS: SULFACETAMIDE SODIUM 100 mg/1 g
INACTIVE INGREDIENTS: GLYCERIN; GLYCERYL MONOSTEARATE; PEG-100 STEARATE; PHENOXYETHANOL; BUTYLATED HYDROXYTOLUENE; TRIACETIN; SODIUM THIOSULFATE; STEARYL ALCOHOL; CETYL ALCOHOL; COCAMIDOPROPYL BETAINE; EDETATE DISODIUM ANHYDROUS; CITRIC ACID MONOHYDRATE; WATER; SODIUM LAURETH SULFATE; XANTHAN GUM

Sodium Sulfacetamide 10%

Inactive Ingredients

Butylated Hydroxytoluene, Citric Acid, Cetyl Alcohol, Cocamidopropyl Betaine, Disodium EDTA, Glycerin, Glyceryl Stearate SE, PEG-100 Stearate, Phenoxyethanol, Purified Water, Sodium Laureth Sulfate, Sodium Thiosulfate, Stearyl Alcohol, Triacetin, Xanthan Gum.

Description

Each gram contains 100 mg of sodium sulfacetamide in a vehicle consisting of:
Butylated Hydroxytoluene, Citric Acid, Cetyl Alcohol, Cocamidopropyl Betaine, Disodium EDTA, Glycerin, Glyceryl Stearate SE, PEG-100 Stearate, Phenoxyethanol, Purified Water, Sodium Laureth Sulfate, Sodium Thiosulfate, Stearyl Alcohol, Triacetin, Xanthan Gum.

Indications

This product is intended for topical application in the following scaling dermatoses: seborrheic dermatitis and seborrhea sicca (dandruff). It also is indicated for the treatment of secondary bacterial infections of the skin due to organisms susceptible to sulfonamides.

Contraindications

This product is contraindicated in persons with known or suspected hypersensitivity to any of the ingredients of the product. This product is not to be used by patients with kidney disease.

Dosage and Administration

Seborrheic dermatitis including seborrhea sicca - Wash affected areas twice daily (morning and evening) or as directed by your physician. Avoid contact with eyes or mucous membranes. Wet skin and liberally apply to areas to be cleansed, massage gently into skin working into a full lather, rinse thoroughly, pat dry and repeat after 10 to 20 seconds. Rinsing with plain water will remove any excess medication. Repeat application as described above for 8 to 10 days or as directed by your physician. lf skin dryness occurs it may be controlled by rinsing cleanser off sooner or using less frequently. Regular shampooing following the use of this product is not necessary, but the hair should be shampooed at least once a week. As the condition subsides, the interval between
applications may be lengthened. Applications once or twice weekly or every other week may prevent recurrence. Should the condition recur after stopping therapy, the application of this product should be reinitiated as at the beginning of treatment.

Secondary cutaneous bacterial infections - Wash affected areas twice daily (morning and evening) or as directed by your physician. Avoid contact with eyes or mucous membranes. Wet skin and liberally apply to areas to be cleansed, massage gently into skin for 10 to 20 seconds working into a full lather, rinse thoroughly and pat dry. Rinsing with plain water will remove any excess medication. Repeat application as described above for 8 to 10 days or as directed by your physician. If skin dryness occurs it may be controlled by rinsing cleanser off sooner or using less frequently. See package insert for full prescribing information.

Warnings

WARNING: FOR EXTERNAL USE ONLY. NOT FOR OPHTHALMIC USE.
KEEP OUT OF REACH OF CHILDREN.

Avoid contact with eyes, lips and mucous membranes.

See label booklet for Full prescribing information.

Storage

Store at 20°C to 25°C (68°F to 77°F), excursions permitted between 15°C and 30°C (between 59°F and 86°F). Protect from freezing and excessive heat. Keep bottle tightly closed.

This bottle is not filled to the top but does contain 6 fl oz of product as identified on the front
panel of the bottle.

To report a serious adverse event or obtain product information, call (877) 250-3427.

Package

Manufactured in the U.S.A. for
Method Pharmaceuticals, LLC
Southlake, Texas 76092
Rev 09/21